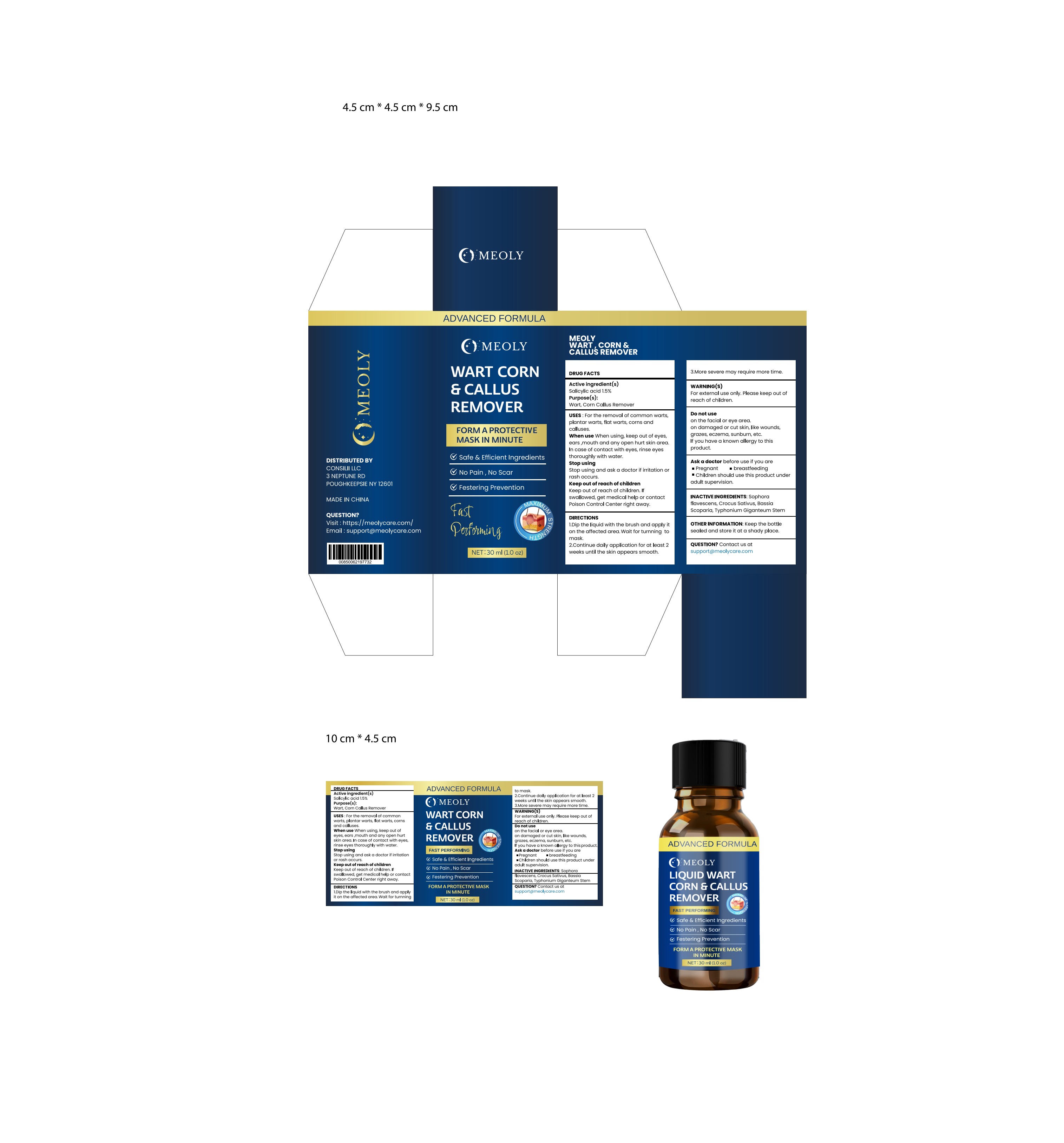 DRUG LABEL: MEOLY Wart Corn Remover
NDC: 83818-006 | Form: LIQUID
Manufacturer: Shenzhen Xinxin Yunhai Technology Co., Ltd.
Category: otc | Type: HUMAN OTC DRUG LABEL
Date: 20241106

ACTIVE INGREDIENTS: SALICYLIC ACID 1.5 g/100 mL
INACTIVE INGREDIENTS: PARAFFIN; LANOLIN; C18-38 ALKYL HYDROXYSTEAROYL STEARATE; VASOPRESSIN; PHENOL

83818-006

Active Ingredient

alicylic acid1.5%

Purpose

wart,corn callus Remover

Use

or the removal of common wartsont
plantar warts,flat warts,corns and calluses

Warnings

For external use only. Please keep out ofreach of children.

Do not use

on the facial or eye area.on damaged or cut skin, like wounds.grazes, eczema, sunburn, etc.If you have a known allergy to thisproduct.

When Using

when using, keep out of eyes,ears ,mouth and any open hurt skin area.In case of contact with eyes, rinse eyesthoroughly with water.

Stop Use

Stop using and ask a doctor if irritation orrash occurs.

Ask Doctor

Stop using and ask a doctor if irritation orrash occurs.

Keep Oot Of Reach Of Children

Keep out of reach of children. ifswallowed, get medical help or contactPoison Control Center right away.

Directions

1.Dip the liquid with the brush and apply iton the affected area.Wait for turnning tomask.
2.Continue daily application for at least 2weeks until the skin appears smooth.

3.More severe may require more time.

Other information

Keep the bottlesealed and store it at a shady place.

Inactive ingredients

Sophoraflavescens, Crocus Sativus, Bassiascoparia, Typhonium Giganteum Stem

Questions

Contact us atsupport@meolycare.com